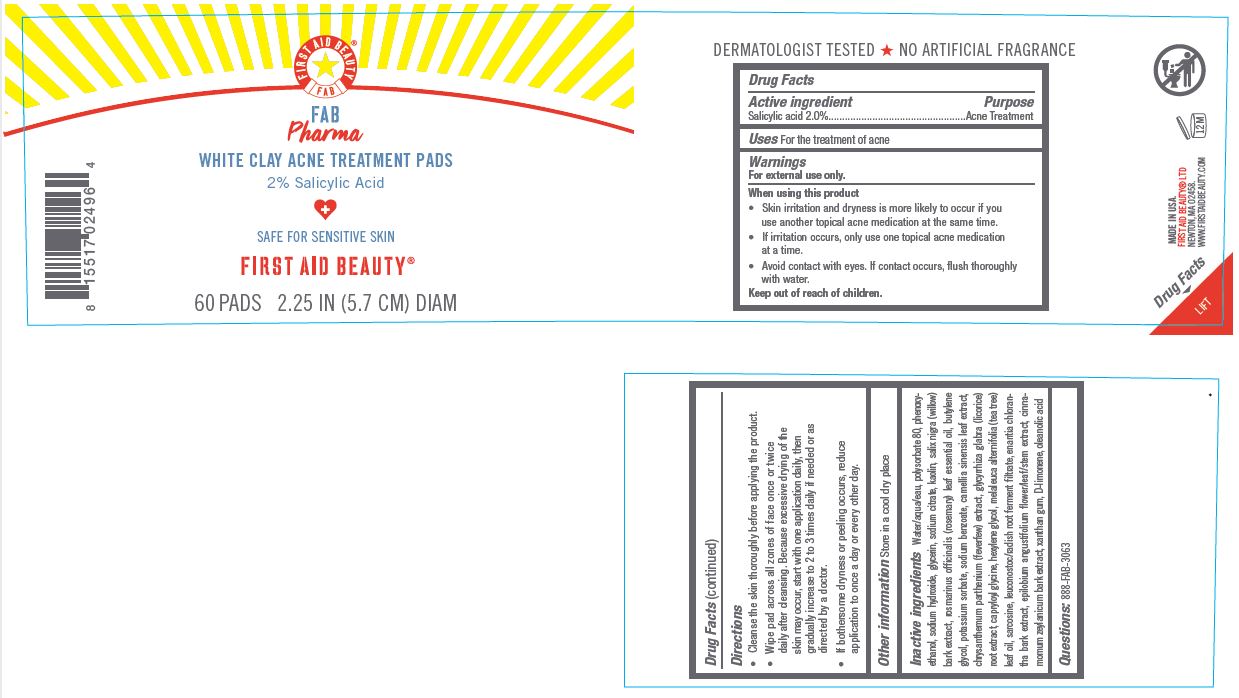 DRUG LABEL: First Aid Beauty FAB Pharma White Clay Acne Treatment
NDC: 69423-555 | Form: DISC
Manufacturer: The Procter & Gamble Manufacturing Company
Category: otc | Type: HUMAN OTC DRUG LABEL
Date: 20251218

ACTIVE INGREDIENTS: SALICYLIC ACID 2 g/100 mL
INACTIVE INGREDIENTS: CAPRYLOYL GLYCINE; ROSEMARY OIL; EPILOBIUM ANGUSTIFOLIUM FLOWERING TOP; CINNAMON BARK OIL; XANTHAN GUM; OLEANOLIC ACID; LIMONENE, (+)-; TEA TREE OIL; KAOLIN; HEXYLENE GLYCOL; ANNICKIA CHLORANTHA BARK; SODIUM HYDROXIDE; SODIUM CITRATE; BUTYLENE GLYCOL; PHENOXYETHANOL; TANACETUM PARTHENIUM FLOWER; GLYCYRRHIZA GLABRA; LEUCONOSTOC/RADISH ROOT FERMENT FILTRATE; GREEN TEA LEAF; POLYSORBATE 80; WATER; GLYCERIN; POTASSIUM SORBATE; SODIUM BENZOATE; SARCOSINE; SALIX NIGRA BARK

First Aid Beauty FAB Pharma White Clay Acne Treatment

Drug Facts

Active ingredients

Salicylic Acid 2%

Purpose

Acne Treatment

Uses

- for the treatment of acne

Warnings

For external use only.

WHEN USING

Skin irritation and dryness is more likely to occur if you use another topical acne medication at the same time.

If irritation occurs, only use one topical acne medication at a time.

Avoid contact with eyes. If contact occurs, rinse eyes thoroughly with water.

Keep out of reach of children. If swallowed, get medical help or contact a Poison Control Center right away.

Directions

• Cleanse the skin thoroughly before applying the product.
• Wipe pad across all zones of face once or twice daily after cleansing. Because excessive drying of the skin may occur, start with one application daily, then gradually increase to 2 to 3 times daily if needed or as directed by a doctor.
If bothersome dryness or peeling occurs, reduce application to once a day or every other day.

INACTIVE INGREDIENT

Water/aqua/eau, polysorbate 80, phenoxyethanol, sodium hydroxide, glycerin, sodium citrate, kaolin, salix nigra (willow) bark extract, rosmarinus officinalis (rosemary) leaf essential oil, butylene glycol, potassium sorbate, sodium benzoate, camellia sinensis leaf extract, chrysanthemum parthenium (feverfew) extract, glycyrrhiza glabra (licorice) root extract, capryloyl glycine, hexylene glycol, melaleuca alternifolia (tea tree) leaf oil, sarcosine, leuconostoc/radish root ferment filtrate, enantia chlorantha bark extract, epilobium angustifolium flower/leaf/stem extract, cinnamomum zeylanicum bark extract, xanthan gum, D-limonene, oleanolic acid

Questions:

888-FAB-3063

MADE IN USA

FIRST AID BEAUTY LTD

NEWTON, MA 02458

WWW.FIRSTAIDBEAUTY.COM

PRINCIPAL DISPLAY PANEL - 60 pads carton

First Aid Beauty

FAB

Pharma

White Clay Acne Treatment Pads

2% Salicylic Acid

Safe for sensitive skin

FIrst Aid Beauty ®

60 PADS 2.25 IN (5.7 CM) DIAM